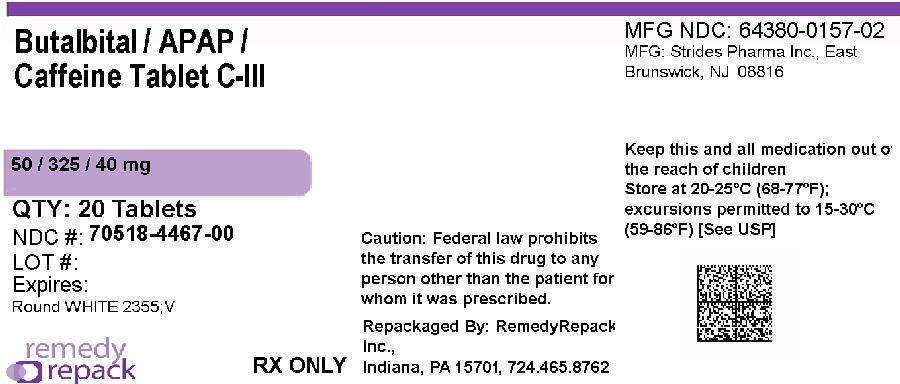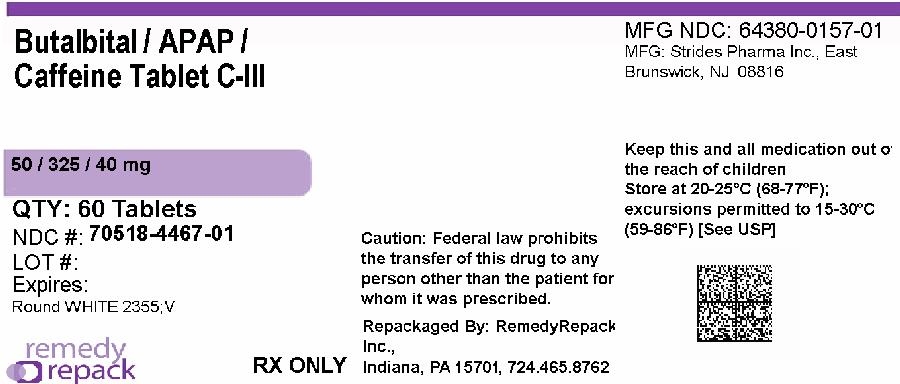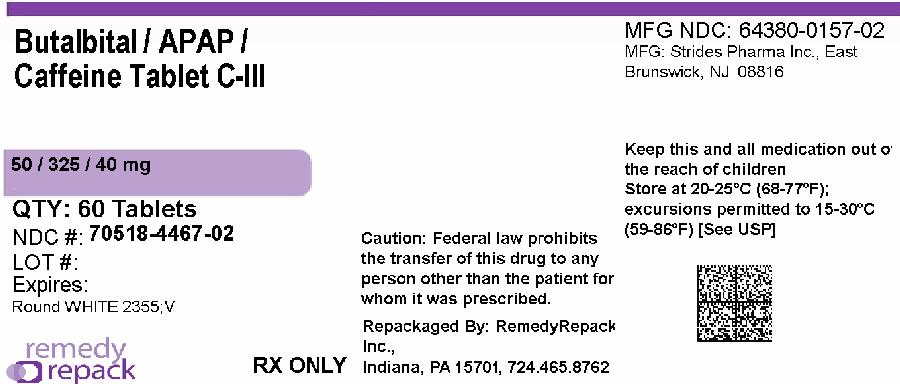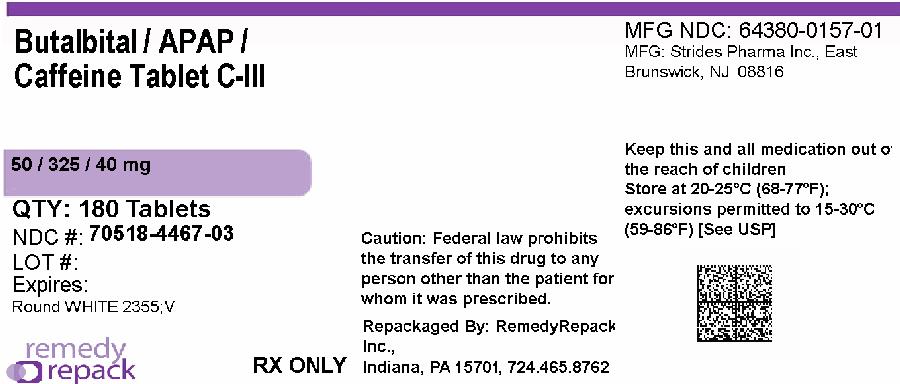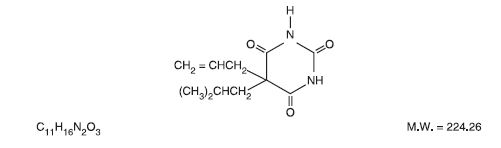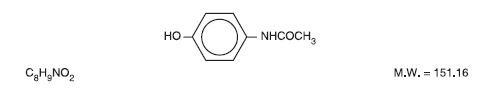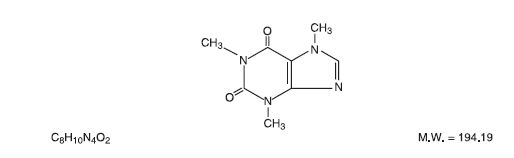 DRUG LABEL: Butalbital, Acetaminophen and Caffeine
NDC: 70518-4467 | Form: TABLET
Manufacturer: REMEDYREPACK INC.
Category: prescription | Type: HUMAN PRESCRIPTION DRUG LABEL
Date: 20260127
DEA Schedule: CIII

ACTIVE INGREDIENTS: BUTALBITAL 50 mg/1 1; ACETAMINOPHEN 325 mg/1 1; CAFFEINE 40 mg/1 1
INACTIVE INGREDIENTS: SILICON DIOXIDE; CROSCARMELLOSE SODIUM; MAGNESIUM STEARATE; CELLULOSE, MICROCRYSTALLINE; STEARIC ACID; CROSPOVIDONE; POVIDONE; STARCH, CORN

Butalbital, Acetaminophen and Caffeine Tablets, USP CIII
50 mg/325 mg/40 mg

BOXED WARNING

Hepatotoxicity

Acetaminophen has been associated with cases of acute liver failure, at times resulting in liver transplant and death. Most of the cases of liver injury are associated with the use of acetaminophen at doses that exceed 4000 milligrams per day, and often involve more than one acetaminophen-containing product.

DESCRIPTION

Butalbital, Acetaminophen and Caffeine Tablets, USP are supplied in tablet form for oral administration.

Each tablet contains the following active ingredients:

butalbital, USP ...................................................................................... 50 mg

acetaminophen, USP ........................................................................... 325 mg

caffeine, USP ........................................................................................ 40 mg

Inactive Ingredients:colloidal silicon dioxide, croscarmellose sodium, crospovidone, magnesium stearate, microcrystalline cellulose, povidone, pregelatinized starch, and stearic acid.

Butalbital (5-allyl-5-isobutylbarbituric acid), is a short to intermediate-acting barbiturate. It has the following structural formula:

Acetaminophen (4'-hydroxyacetanilide), is a non-opiate, non-salicylate analgesic and antipyretic. It has the following structural formula.

Caffeine (1,3,7-trimethylxanthine), is a central nervous system stimulant. It has the following structural formula:

CLINICAL PHARMACOLOGY

This combination drug product is intended as a treatment for tension headache.

It consists of a fixed combination of butalbital, acetaminophen and caffeine. The role each component plays in the relief of the complex of symptoms known as tension headache is incompletely understood.

Pharmacokinetics

The behavior of the individual components is described below.

Butalbital

Butalbital is well absorbed from the gastrointestinal tract and is expected to distribute to most tissues in the body. Barbiturates in general may appear in breast milk and readily cross the placental barrier. They are bound to plasma and tissue proteins to a varying degree and binding increases directly as a function of lipid solubility.

Elimination of butalbital is primarily via the kidney (59% to 88% of the dose) as unchanged drug or metabolites. The plasma half-life is about 35 hours. Urinary excretion products include parent drug (about 3.6% of the dose), 5-isobutyl-5-(2, 3-dihydroxypropyl) barbituric acid (about 24% of the dose), 5-allyl-5(3-hydroxy-2-methyl-1-propyl) barbituric acid (about 4.8% of the dose), products with the barbituric acid ring hydrolyzed with excretion of urea (about 14% of the dose), as well as unidentified materials. Of the material excreted in the urine, 32% is conjugated.

The in vitroplasma protein binding of butalbital is 45% over the concentration range of 0.5 to 20 mcg/mL. This falls within the range of plasma protein binding (20% to 45%) reported with other barbiturates such as phenobarbital, pentobarbital, and secobarbital sodium. The plasma-to-blood concentration ratio was almost unity, indicating that there is no preferential distribution of butalbital into either plasma or blood cells.

See OVERDOSAGE for toxicity information.

Acetaminophen

Acetaminophen is rapidly absorbed from the gastrointestinal tract and is distributed throughout most body tissues. The plasma half-life is 1.25 to 3 hours, but may be increased by liver damage and following overdosage. Elimination of acetaminophen is principally by liver metabolism (conjugation) and subsequent renal excretion of metabolites. Approximately 85% of an oral dose appears in the urine within 24 hours of administration, most as the glucuronide conjugate, with small amounts of other conjugates and unchanged drug.

See OVERDOSAGE for toxicity information.

Caffeine

Like most xanthines, caffeine is rapidly absorbed and distributed in all body tissues and fluids, including the CNS, fetal tissues, and breast milk.

Caffeine is cleared through metabolism and excretion in the urine. The plasma half-life is about 3 hours. Hepatic biotransformation prior to excretion results in about equal amounts of 1-methylxanthine and 1-methyluric acid. Of the 70% of the dose that is recovered in the urine, only 3% is unchanged drug.

See OVERDOSAGE for toxicity information.

INDICATIONS AND USAGE

Butalbital, acetaminophen and caffeine tablets are indicated for the relief of the symptom complex of tension (or muscle contraction) headache.

Evidence supporting the efficacy and safety of this combination product in the treatment of multiple recurrent headaches is unavailable. Caution in this regard is required because butalbital is habit-forming and potentially abusable.

CONTRAINDICATIONS

This product is contraindicated under the following conditions:

– Hypersensitivity or intolerance to any component of this product

– Patients with porphyria.

WARNINGS

Hepatotoxicity

Acetaminophen has been associated with cases of acute liver failure, at times resulting in liver transplant and death. Most of the cases of liver injury are associated with the use of acetaminophen at doses that exceed 4000 milligrams per day, and often involve more than one acetaminophen-containing product. The excessive intake of acetaminophen may be intentional to cause self-harm or unintentional as patients attempt to obtain more pain relief or unknowingly take other acetaminophen-containing products.

The risk of acute liver failure is higher in individuals with underlying liver disease and in individuals who ingest alcohol while taking acetaminophen.

Instruct patients to look for acetaminophen or APAP on package labels and not to use more than one product that contains acetaminophen. Instruct patients to seek medical attention immediately upon ingestion of more than 4000 milligrams of acetaminophen per day, even if they feel well.

Serious skin reactions

Rarely, acetaminophen may cause serious skin reactions such as acute generalized exanthematous pustulosis (AGEP), Stevens-Johnson Syndrome (SJS), and toxic epidermal necrolysis (TEN), which can be fatal. Patients should be informed about the signs of serious skin reactions, and use of the drug should be discontinued at the first appearance of skin rash or any other sign of hypersensitivity.

Hypersensitivity/anaphylaxis

There have been post-marketing reports of hypersensitivity and anaphylaxis associated with use of acetaminophen. Clinical signs included swelling of the face, mouth, and throat, respiratory distress, urticaria, rash, pruritus, and vomiting. There were infrequent reports of life-threatening anaphylaxis requiring emergency medical attention. Instruct patients to discontinue Butalbital, Acetaminophen and Caffeine Tablets, USP immediately and seek medical care if they experience these symptoms. Do not prescribe Butalbital, Acetaminophen and Caffeine Tablets, USP for patients with acetaminophen allergy.

Butalbital is habit-forming and potentially abusable. Consequently, the extended use of this product is not recommended.

PRECAUTIONS

General

Butalbital, acetaminophen and caffeine tablets should be prescribed with caution in certain special-risk patients, such as the elderly or debilitated, and those with severe impairment of renal or hepatic function, or acute abdominal conditions.

Information for Patients/Caregivers

- Do not take Butalbital, Acetaminophen and Caffeine Tablets, USP if you are allergic to any of its ingredients.
- If you develop signs of allergy such as a rash or difficulty breathing stop taking Butalbital, Acetaminophen and Caffeine Tablets, USP and contact your healthcare provider immediately.
- Do not take more than 4000 milligrams of acetaminophen per day. Call your doctor if you took more than the recommended dose.

This product may impair mental and/or physical abilities required for the performance of potentially hazardous tasks such as driving a car or operating machinery. Such tasks should be avoided while taking this product.

Alcohol and other CNS depressants may produce an additive CNS depression, when taken with this combination product, and should be avoided.

Butalbital may be habit-forming. Patients should take the drug only for as long as it is prescribed, in the amounts prescribed, and no more frequently than prescribed.

For information on use in geriatric patients, see PRECAUTIONS/Geriatric Use.

Laboratory Tests

In patients with severe hepatic or renal disease, effects of therapy should be monitored with serial liver and/or renal function tests.

Drug Interactions

The CNS effects of butalbital may be enhanced by monoamine oxidase (MAO) inhibitors.

Butalbital, acetaminophen and caffeine may enhance the effects of: other narcotic analgesics, alcohol, general anesthetics, tranquilizers such as chlordiazepoxide, sedative-hypnotics, or other CNS depressants, causing increased CNS depression.

Drug/Laboratory Test Interactions

Acetaminophen may produce false-positive test results for urinary 5-hydroxyindoleacetic acid.

Carcinogenesis, Mutagenesis, Impairment of Fertility

No adequate studies have been conducted in animals to determine whether acetaminophen or butalbital have a potential for carcinogenesis, mutagenesis or impairment of fertility.

Pregnancy

Teratogenic Effects

Pregnancy Category C:Animal reproduction studies have not been conducted with this combination product. It is also not known whether butalbital, acetaminophen and caffeine can cause fetal harm when administered to a pregnant woman or can affect reproduction capacity. This product should be given to a pregnant woman only when clearly needed.

Nonteratogenic Effects

Withdrawal seizures were reported in a two-day-old male infant whose mother had taken a butalbital-containing drug during the last two months of pregnancy. Butalbital was found in the infant's serum. The infant was given phenobarbital 5 mg/kg, which was tapered without further seizure or other withdrawal symptoms.

Nursing Mothers

Caffeine, barbiturates and acetaminophen are excreted in breast milk in small amounts, but the significance of their effects on nursing infants is not known. Because of potential for serious adverse reactions in nursing infants from butalbital, acetaminophen and caffeine, a decision should be made whether to discontinue nursing or to discontinue the drug, taking into account the importance of the drug to the mother.

Pediatric Use

Safety and effectiveness in pediatric patients below the age of 12 have not been established.

Geriatric Use

Clinical studies of butalbital, acetaminophen and caffeine tablets did not include sufficient numbers of subjects aged 65 and over to determine whether they respond differently from younger subjects. Other reported clinical experience has not identified differences in responses between the elderly and younger patients. In general, dose selection for an elderly patient should be cautious, usually starting at the low end of the dosing range, reflecting the greater frequency of decreased hepatic, renal, or cardiac function, and of concomitant disease or other drug therapy.

Butalbital is known to be substantially excreted by the kidney, and the risk of toxic reactions to this drug may be greater in patients with impaired renal function. Because elderly patients are more likely to have decreased renal function, care should be taken in dose selection, and it may be useful to monitor renal function.

ADVERSE REACTIONS

Frequently Observed

The most frequently reported adverse reactions are drowsiness, lightheadedness, dizziness, sedation, shortness of breath, nausea, vomiting, abdominal pain, and intoxicated feeling.

Infrequently Observed

All adverse events tabulated below are classified as infrequent.

Central Nervous System:headache, shaky feeling, tingling, agitation, fainting, fatigue, heavy eyelids, high energy, hot spells, numbness, sluggishness, seizure. Mental confusion, excitement, or depression can also occur due to intolerance, particularly in elderly or debilitated patients, or due to overdosage of butalbital.

Autonomic Nervous System:dry mouth, hyperhidrosis.

Gastrointestinal:difficulty swallowing, heartburn, flatulence, constipation.

Cardiovascular:tachycardia.

Musculoskeletal:leg pain, muscle fatigue.

Genitourinary:diuresis.

Miscellaneous:pruritus, fever, earache, nasal congestion, tinnitus, euphoria, allergic reactions.

Several cases of dermatological reactions, including toxic epidermal necrolysis and erythema multiforme, have been reported.

The following adverse drug events may be borne in mind as potential effects of the components of this product. Potential effects of high dosage are listed in the OVERDOSAGEsection.

Acetaminophen:allergic reactions, rash, thrombocytopenia, agranulocytosis.

Caffeine:cardiac stimulation, irritability, tremor, dependence, nephrotoxicity, hyperglycemia.

To report SUSPECTED ADVERSE REACTIONS, contact Strides Pharma Inc. at 1-877-244-9825 or go to www.strides.com or FDA at 1-800-FDA-1088 or www.fda.gov/medwatch.

DRUG ABUSE AND DEPENDENCE

Abuse and Dependence

Butalbital

Barbiturates may be habit-forming:Tolerance, psychological dependence, and physical dependence may occur especially following prolonged use of high doses of barbiturates. The average daily dose for the barbiturate addict is usually about 1500 mg. As tolerance to barbiturates develops, the amount needed to maintain the same level of intoxication increases; tolerance to a fatal dosage, however, does not increase more than two-fold. As this occurs, the margin between an intoxication dosage and fatal dosage becomes smaller. The lethal dose of a barbiturate is far less if alcohol is also ingested. Major withdrawal symptoms (convulsions and delirium) may occur within 16 hours and last up to 5 days after abrupt cessation of these drugs. Intensity of withdrawal symptoms gradually declines over a period of approximately 15 days. Treatment of barbiturate dependence consists of cautious and gradual withdrawal of the drug. Barbiturate-dependent patients can be withdrawn by using a number of different withdrawal regimens. One method involves initiating treatment at the patient's regular dosage level and gradually decreasing the daily dosage as tolerated by the patient.

OVERDOSAGE

Following an acute overdosage of butalbital, acetaminophen and caffeine, toxicity may result from the barbiturate or the acetaminophen. Toxicity due to caffeine is less likely, due to the relatively small amounts in this formulation.

Signs and Symptoms

Toxicity from barbituratepoisoning includes drowsiness, confusion, and coma; respiratory depression; hypotension; and hypovolemic shock.

In acetaminophenoverdosage: dose-dependent, potentially fatal hepatic necrosis is the most serious adverse effect. Renal tubular necroses, hypoglycemic coma and coagulation defects may also occur. Early symptoms following a potentially hepatotoxic overdose may include: nausea, vomiting, diaphoresis and general malaise. Clinical and laboratory evidence of hepatic toxicity may not be apparent until 48 to 72 hours post-ingestion.

Acute caffeinepoisoning may cause insomnia, restlessness, tremor, and delirium, tachycardia and extrasystoles.

Treatment

A single or multiple drug overdose with this combination product is a potentially lethal polydrug overdose, and consultation with a regional poison control center is recommended. Immediate treatment includes support of cardiorespiratory function and measures to reduce drug absorption.

Oxygen, intravenous fluids, vasopressors, and other supportive measures should be employed as indicated. Assisted or controlled ventilation should also be considered.

Gastric decontamination with activated charcoal should be administered just prior to N-acetylcysteine (NAC) to decrease systemic absorption if acetaminophen ingestion is known or suspected to have occurred within a few hours of presentation. Serum acetaminophen levels should be obtained immediately if the patient presents 4 hours or more after ingestion to assess potential risk of hepatotoxicity; acetaminophen levels drawn less than 4 hours post-ingestion may be misleading. To obtain the best possible outcome, NAC should be administered as soon as possible where impending or evolving liver injury is suspected. Intravenous NAC may be administered when circumstances preclude oral administration.

Vigorous supportive therapy is required in severe intoxication. Procedures to limit the continuing absorption of the drug must be readily performed since the hepatic injury is dose dependent and occurs early in the course of intoxication.

DOSAGE AND ADMINISTRATION

One or 2 tablets every 4 hours as needed. Total daily dosage should not exceed 6 tablets.

Extended and repeated use of this product is not recommended because of the potential for physical dependence.

HOW SUPPLIED

Butalbital, Acetaminophen and Caffeine Tablets, USP

Containing 50 mg butalbital, 325 mg acetaminophen and 40 mg caffeine. Available as white, round shaped tablets, debossed "2355" on one side, and debossed "V" on the reverse side.

NDC: 70518-4467-00

NDC: 70518-4467-01

NDC: 70518-4467-02

NDC: 70518-4467-03

PACKAGING: 20 in 1 BOTTLE PLASTIC

PACKAGING: 60 in 1 BOTTLE PLASTIC

PACKAGING: 60 in 1 BOTTLE PLASTIC

PACKAGING: 180 in 1 BOTTLE PLASTIC

Store and Dispense

Store at 20° to 25°C (68° to 77°F) with excursions permitted between 15° to 30°C (59° to 86°F) [see USP Controlled Room Temperature]; dispense in a tight, light-resistant container as defined in the USP.

Repackaged and Distributed By:

Remedy Repack, Inc.

625 Kolter Dr. Suite #4 Indiana

PACKAGE LABEL

DRUG: Butalbital, Acetaminophen and Caffeine

GENERIC: Butalbital, Acetaminophen, and Caffeine

DOSAGE: TABLET

ADMINSTRATION: ORAL

NDC: 70518-4467-00

NDC: 70518-4467-01

NDC: 70518-4467-02

NDC: 70518-4467-03

COLOR: white

SHAPE: ROUND

SCORE: No score

SIZE: 11 mm

IMPRINT: 2355;V

PACKAGING: 20 in 1 BOTTLE PLASTIC

PACKAGING: 60 in 1 BOTTLE PLASTIC

PACKAGING: 60 in 1 BOTTLE PLASTIC

PACKAGING: 180 in 1 BOTTLE PLASTIC

ACTIVE INGREDIENT(S):

- CAFFEINE 40mg in 1
- BUTALBITAL 50mg in 1
- ACETAMINOPHEN 325mg in 1

INACTIVE INGREDIENT(S):

- SILICON DIOXIDE
- CROSCARMELLOSE SODIUM
- MAGNESIUM STEARATE
- CELLULOSE, MICROCRYSTALLINE
- STEARIC ACID
- CROSPOVIDONE
- POVIDONE
- STARCH, CORN